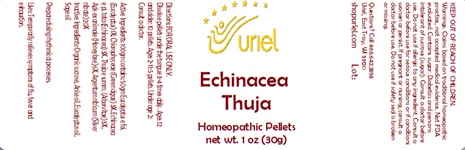 DRUG LABEL: Echinacea Thuja
NDC: 48951-4133 | Form: PELLET
Manufacturer: Uriel Pharmacy Inc
Category: homeopathic | Type: HUMAN OTC DRUG LABEL
Date: 20241203

ACTIVE INGREDIENTS: EUCALYPTUS GLOBULUS LEAF 1 [hp_X]/1 1; ECHINACEA PALLIDA 3 [hp_X]/1 1; THUJA OCCIDENTALIS LEAFY TWIG 3 [hp_X]/1 1; APIS MELLIFERA 6 [hp_X]/1 1; SILVER NITRATE 20 [hp_X]/1 1
INACTIVE INGREDIENTS: EUCALYPTUS OIL; ANISE OIL; SAGE OIL; SUCROSE

Echinacea Thuja

INDICATIONS AND USAGE

Directions: FOR ORAL USE ONLY.

DOSAGE AND ADMINISTRATION

Dissolve pellets under the tongue 3-4
times daily. Ages 12 and older: 10 pellets. Ages 2-11: 5 pellets. Under age 2: Consult
a doctor.

ACTIVE INGREDIENT

Active Ingredients: 100gm contains: 50gm Eucalyptus e fol. (Eucalyptus) 1X; Chlorophyceae (Green algae) 3X, Echinacea e pl. tota (Echinacea) 3X, Thuja e summ. (Arborvitae) 3X, Apis ex animale (Honeybee) 6X, Argentum nitricum (Silver nitrate) 20X

INACTIVE INGREDIENT

Inactive Ingredients: Organic sucrose, Anise oil, Eucalyptus oil, Sage oil

Prepared using rhythmical processes.

PURPOSE

Uses: Temporarily relieves symptoms of flu, fever and exhaustion.

KEEP OUT OF REACH OF CHILDREN.

WARNINGS

Warnings: Claims based on traditional homeopathic practice, not accepted medical evidence. Not FDA evaluated. Contains sugar. Diabetics and persons intolerant of sucrose (sugar): Consult a doctor before use. Do not use if allergic to any ingredient. Consult a doctor before use for serious conditions or if conditions worsen or persist. If pregnant or nursing, consult a doctor before use. Do not use if safety seal is broken or missing.

Questions? Call 866.642.2858
Uriel, East Troy, WI 53120
shopuriel.com Lot: